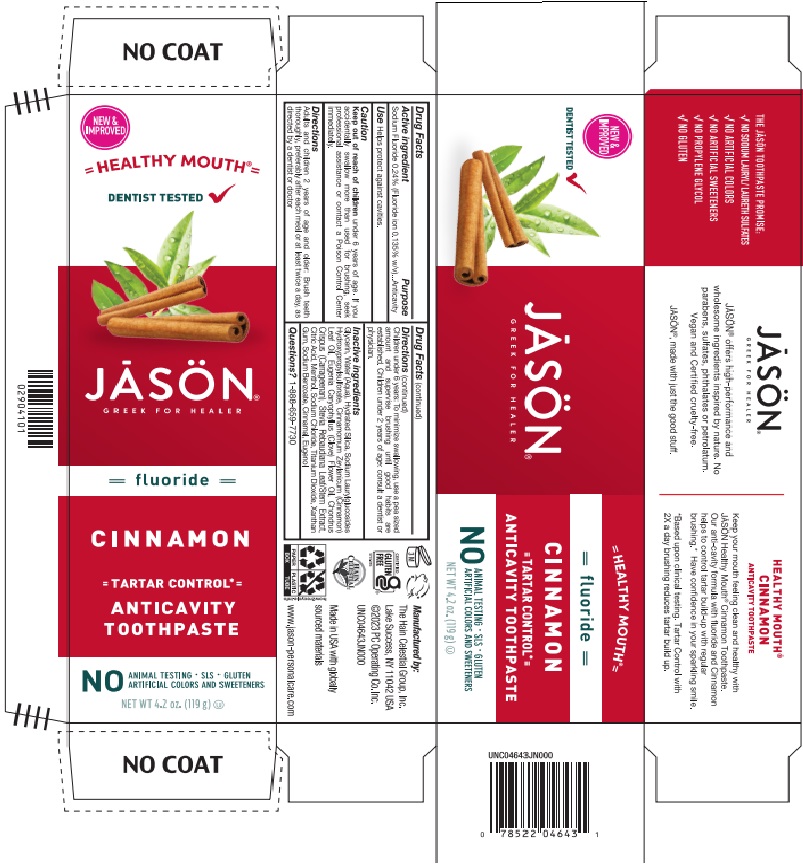 DRUG LABEL: Jason Healthy Mouth Fluoride Cinnamon Anticavity
NDC: 61995-0603 | Form: GEL
Manufacturer: The Hain Celestial Group, Inc.
Category: otc | Type: HUMAN OTC DRUG LABEL
Date: 20241128

ACTIVE INGREDIENTS: SODIUM FLUORIDE 0.24 g/100 g
INACTIVE INGREDIENTS: GLYCERIN; WATER; HYDRATED SILICA; SODIUM LAURYLGLUCOSIDES HYDROXYPROPYLSULFONATE; TITANIUM DIOXIDE; CINNAMON OIL; CARRAGEENAN; ANHYDROUS CITRIC ACID; STEVIA REBAUDIUNA LEAF; MENTHOL, (+)-; SODIUM CHLORIDE; XANTHAN GUM; SODIUM BENZOATE; CLOVE OIL; EUGENOL

Jason Healthy Mouth Anticavity Cinnamon Toothpaste

ACTIVE INGREDIENT

Sodium Fluoride 0.24%

PURPOSE

Anticavity

INDICATIONS AND USAGE

use: Prevention of cavities

WARNINGS

Avoid storing at high temperatures (greater than 100°F). Protect from freezing. If you accidentally swalow more than used for brushing, seek professional assistance or contact Poison Control immediately.

Keep out of reach of children under 6 years of age.If you accidentally swallow more than used for brushing, get medical help or contact Poison Control Center immediately.

DOSAGE AND ADMINISTRATION

Prevent plaque and tartar buildup with regular brushing. Adults and children 2 years of age or older should brush teeth after each meal (or at least twice a day, or as directed by a dentist or doctor). Children under 6: To minimize swallowing, use a pea sized amount of paste and supervise rushing until good habits are established. Children under 2, check with a dentist or physician before using.

INACTIVE INGREDIENT

Glycerin, Water (Aqua), Hydrated Silica, Sodium Laurylglucosides Hydroxypropylsulfonate, Cinnamomum Zeylanicum (Cinnamon) Leaf Oil, Eugenia Caryophyllus (Clove) Flower Oil, Chondrus Crispus (Carrageenan), Stevia Rebaudiana Leaf/Stem Extract, Citric Acid, Menthol, Sodium Chloride, Titanium Dioxide, Xanthan Gum, Sodium Benzoate, Cinnamal, Eugenol